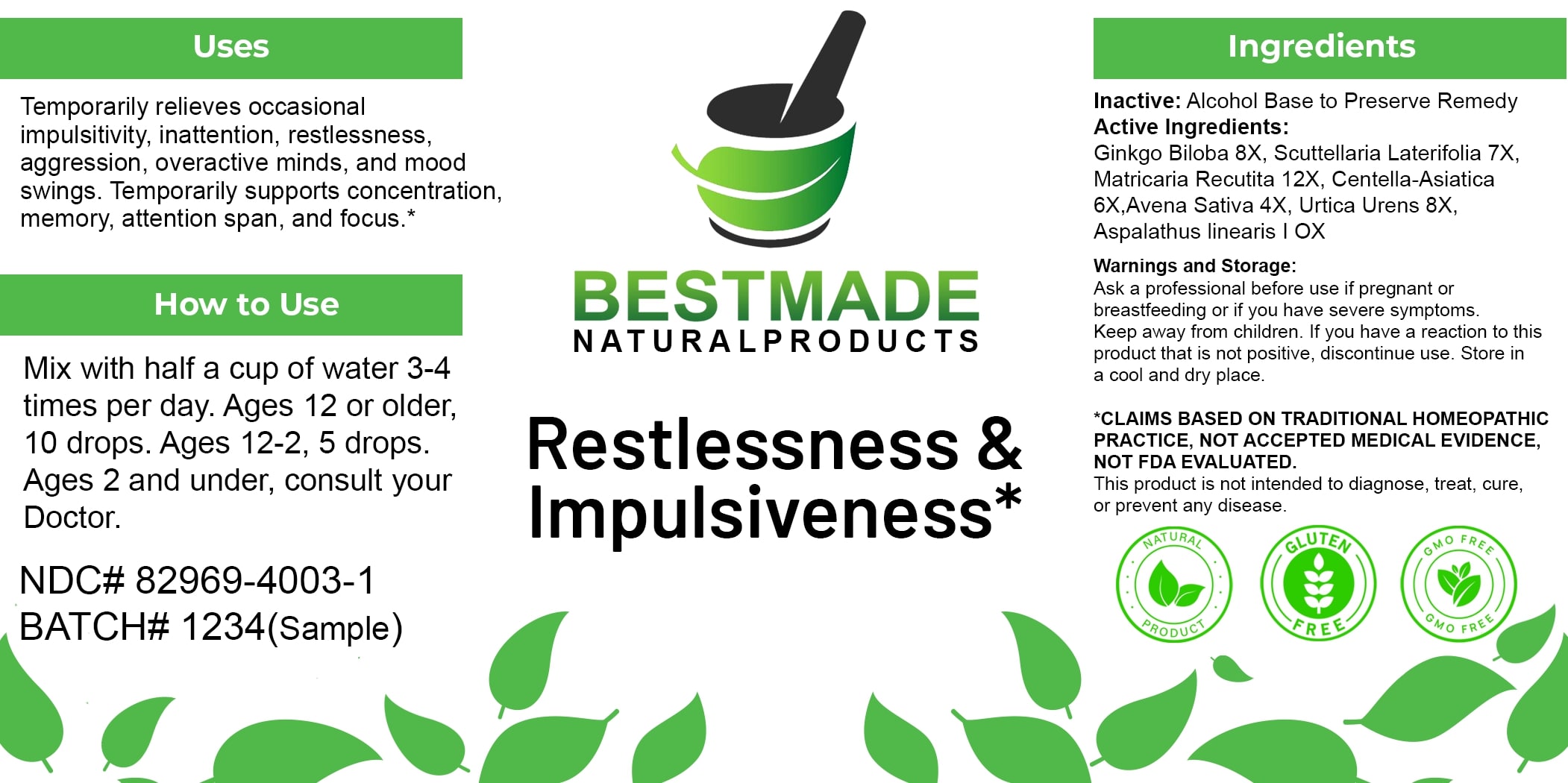 DRUG LABEL: Bestmade Natural Products Restlessness and Impulsiveness
NDC: 82969-4003 | Form: LIQUID
Manufacturer: Bestmade Natural Products
Category: homeopathic | Type: HUMAN OTC DRUG LABEL
Date: 20250307

ACTIVE INGREDIENTS: MATRICARIA RECUTITA 6 [hp_X]/6 [hp_X]; CENTELLA ASIATICA 6 [hp_X]/6 [hp_X]; SCUTELLARIA LATERIFLORA WHOLE 6 [hp_X]/6 [hp_X]; GINKGO 6 [hp_X]/6 [hp_X]; AVENA SATIVA FLOWERING TOP 6 [hp_X]/6 [hp_X]; ASPALATHUS LINEARIS WHOLE 6 [hp_X]/6 [hp_X]; URTICA URENS 6 [hp_X]/6 [hp_X]
INACTIVE INGREDIENTS: ALCOHOL 6 [hp_X]/6 [hp_X]

Hyperactivity & Impulsiveness Solution

DOSAGE AND ADMINISTRATION

How to Use

Mix with half a cup of water 3-4 times per day. Ages 12 or older, 10 drops. Ages 12-2, 5 drops. Ages 2 and under, consult your Doctor.

INACTIVE INGREDIENT

Ingredients

Inactive: Alcohol Base to Preserve Remedy

ACTIVE INGREDIENT

Active Ingredients: Ginkgo Biloba 8X, Scuttellaria Laterifolia 7X, Matricaria Recutita 12X, Centella-Asiatica 6X, Avena Sativa 4X, Urtica Urens 8X, Aspalathus linearis | OX

Uses

Temporarily relieves occasional impulsivity, inattention, restlessness, aggression, overactive minds, and mood swings. Temporarily supports concentration, memory, attention span, and focus.*

*CLAIMS BASED ON TRADITIONAL HOMEOPATHIC PRACTICE, NOT ACCEPTED MEDICAL EVIDENCE, NOT FDA EVALUATED.

This product is not intended to diagnose, treat, cure, or prevent any disease.

Uses

Temporarily relieves occasional impulsivity, inattention, restlessness, aggression, overactive minds, and mood swings. Temporarily supports concentration, memory, attention span, and focus.*

*CLAIMS BASED ON TRADITIONAL HOMEOPATHIC PRACTICE, NOT ACCEPTED MEDICAL EVIDENCE, NOT FDA EVALUATED.

This product is not intended to diagnose, treat, cure, or prevent any disease.

KEEP OUT OF REACH OF CHILDREN

Warnings and Storage:

Ask a professional before use if pregnant or breastfeeding or if you have severe symptoms. Keep away from children. If you have a reaction to this product that is not positive, discontinue use. Store in a cool and dry place.

Warnings and Storage:

Ask a professional before use if pregnant or breastfeeding or if you have severe symptoms. Keep away from children. If you have a reaction to this product that is not positive, discontinue use. Store in a cool and dry place.

*CLAIMS BASED ON TRADITIONAL HOMEOPATHIC PRACTICE, NOT ACCEPTED MEDICAL EVIDENCE, NOT FDA EVALUATED.

This product is not intended to diagnose, treat, cure, or prevent any disease.

Entire package label